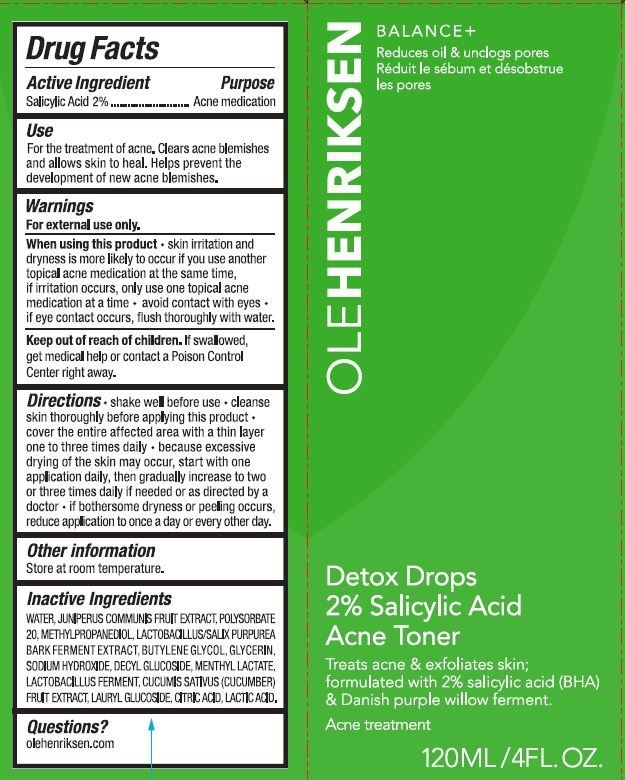 DRUG LABEL: DETOX DROPS ACNE TONER
NDC: 71499-523 | Form: LIQUID
Manufacturer: KENDO HOLDINGS INC.
Category: otc | Type: HUMAN OTC DRUG LABEL
Date: 20250930

ACTIVE INGREDIENTS: SALICYLIC ACID 2 g/100 mL
INACTIVE INGREDIENTS: WATER; JUNIPER BERRY; POLYSORBATE 20; METHYLPROPANEDIOL; SODIUM HYDROXIDE; DECYL GLUCOSIDE; MENTHYL LACTATE; LIMOSILACTOBACILLUS FERMENTUM; CUCUMIS SATIVUS (CUCUMBER) FRUIT; LAURYL GLUCOSIDE; CITRIC ACID; LACTIC ACID; SALIX PURPUREA BARK

ACTIVE INGREDIENT

SALICYLIC ACID 2%

PURPOSE

ACNE TREATMENT

USES

FOR THE TREATMENT OF ACNE. CLEARS ACNE BLEMISHES AND ALLOWS SKIN TO HEAL. HELPS PREVENT THE DEVELOPMENT OF NEW ACNE BLEMISHES.

WARNINGS

FOR EXTERNAL USE ONLY
WHEN USING THIS PRODUCT SKIN IRRITATION AND DRYNESS IS MORE LIKELY TO OCCUR IF YOU USE ANOTHER TOPICAL ACNE MEDICATION AT THE SAME TIME. iF IRRITATION OCCURS, ONLY USE ONE TOPICAL ACNE MEDICATION AT A TIME

AVOID CONTACT WITH EYES. IF EYE CONTACT OCCURS, FLUSH THOROUGHLY WITH WATER.

KEEP OUT OF REACH OF CHILDREN. IF SWALLOWED GET MEICAL HELP OR CONTACT A POISON CONTROL CENTER RIGHT AWAY.

DIRECTIONS

SHAKE WELL BEFORE USE. CLEANSE SKIN THOROUGHLY BEFORE APPLYING THIS PRODUCT.
COVER THE ENTIRE AFFECTED AREA WITH A THIN LAYER ONE TO THREE TIMES DAILY.

BECAUSE EXCESSIVE DRYING OF THE SKIN MAY OCCUR, START WITH ONE APPLICATION DAILY, THEN GRADUALLY INCREASE TO TWO OR THREE TIMES DAILY IF NEEDED OR AS DIRECTED BY A DOCTOR.

IF BOTHERSOME DRYNESS OR PEELING OCCURS REDUCE APPLICATION TO ONCE A DAY OR EVERY OTHER DAY.

OTHER INFORMATION

STORE AT ROOM TEMPERATURE.

INACTIVE INGREDIENTS

WATER, JUNIPERUS COMMUNIS FRUIT EXTRACT, POLYSORBATE 20, METHYLPROPANEDIOL, LACTOBACILLUS/SALIX PURPUREA BARK FERMENT EXTRACT, BUTYLENE GLYCOL, GLYCERIN, SODIUM HYDROXIDE, DECYL GLUCOSIDE, MENTHYL LACTATE, LACTOBACILLUS FERMENT, CUCUMIS SATIVUS (CUCUMBER) FRUIT EXTRACT, LAURYL GLUCOSIDE, CITRIC ACID, LACTIC ACID.

QUESTIONS?

OLEHENRIKSEN.COM